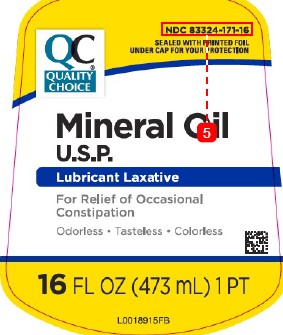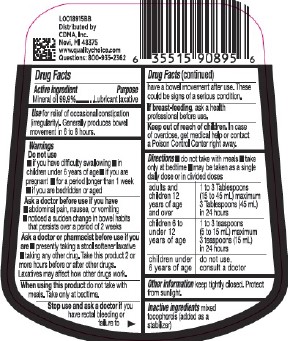 DRUG LABEL: Mineral Oil
NDC: 83324-171 | Form: LIQUID
Manufacturer: Chain Drug Marketing Association
Category: otc | Type: HUMAN OTC DRUG LABEL
Date: 20260227

ACTIVE INGREDIENTS: MINERAL OIL 999 mg/1 mL
INACTIVE INGREDIENTS: TOCOPHEROL

Quality Choice 831.000/831AA
Mineral Oil

Active ingredient

Mineral oil 99.9%

Purpose

Lubricant laxative

Use

for relief of occasional constipation (irregularity). Generally produces bowel movement in 6 to 8 hours.

Do not use

- if you have difficulty swallowing
- in children under 6 years of age
- if you are pregnant
- for a period longer than week
- if you are bedridden or aged

Ask a doctor before use if you have

- abdominal pain, nausea, or vomiting
- noticed a sudden change in bowel habits that persists over a period of 2 weeks

Ask a doctor or pharmacist before use if you are

- presently taking a stool softener laxative
- taking any other drug. Take this product 2 or more hours before or after other drugs. Laxatives may affect how other drugs work.

When using this product

do not take with meals. Take only at bedtime.

Stop use and ask a doctor

if you have rectal bleeding or failure to have a bowel movement after use. These could be signs of a serious condition.

If breast-feeding

ask a health professional before use.

Keep out of reach of children.

in case of overdose, get medical help or contact a Poison Control Center right away.

Directions

- do not take with meals
- take only at bedtime
- may be taken as a single daily dose or in divided doses

adults and children 12 years of age and over - 1 to 3 Tablespoons (15 - 45 mL) maximum 3 Tablespoons (45 mL) in 24 hours

children 6 to under 12 years of age - 1 to 3 teaspoons (5 - 15 mL) maximum 3 teaspoons (15 mL) in 24 hours

children under 6 years of age - do not use, consult a doctor

Other information

keep tightly closed. Protect from sunlight.

Inactive ingredients

mixed tocopherols (added as a stabilizer)

Adverse reaction

Distributed by

CDMA, Inc.

Novi, MI 48375

www.qualitychoice.com

Questions: 800-935-2362

Principal display panel

NDC 83324-171-16

SEALED WITH PRINTED FOIL UNDER CAP FOR YOUR PROTECTION

QC®

QUALITY CHOICE

Mineral OIl

U.S.P.

Lubricant Laxative

For Relief of Occasional Constipation

Odorless - Tasteless - Colorless

16 FL OZ (473 mL) 1 PT